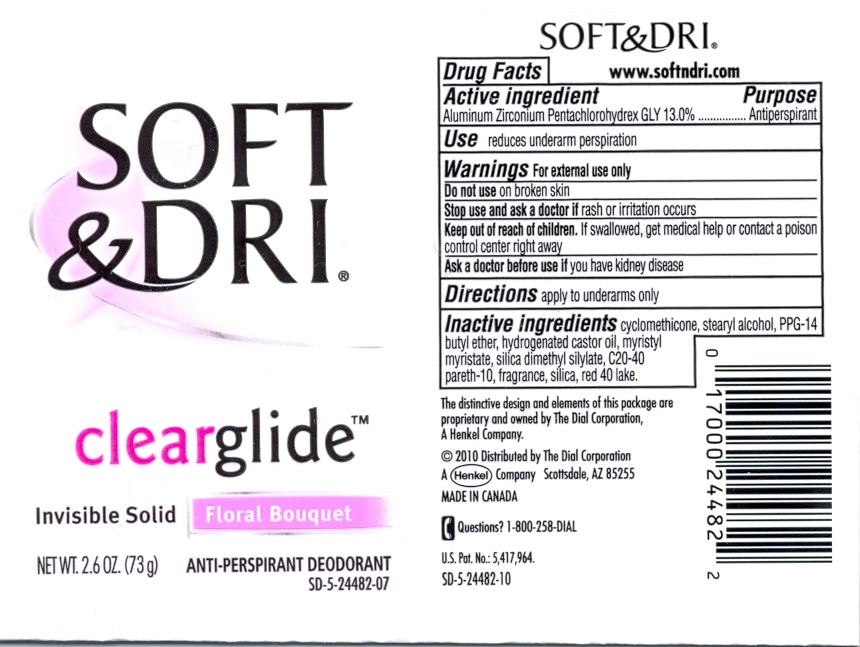 DRUG LABEL: Soft and Dri Clear Glide IS Antiperspirant Floral Bouquet
NDC: 54340-482 | Form: STICK
Manufacturer: The Dial Corporation
Category: otc | Type: HUMAN OTC DRUG LABEL
Date: 20110614

ACTIVE INGREDIENTS: Aluminum Zirconium Pentachlorohydrex Gly 13. g/73 g
INACTIVE INGREDIENTS: CYCLOMETHICONE 5 55.829 g/73 g; SILICON DIOXIDE 0.4329 g/73 g; C20-40 PARETH-10 1.0 g/73 g; HYDROGENATED CASTOR OIL 2.837 g/73 g; MYRISTYL MYRISTATE 1.92 g/73 g; PPG-14 BUTYL ETHER 9.80 g/73 g; STEARYL ALCOHOL 24.0 g/73 g

Soft&Dri ClearGlide Invisible Solid Antiperspirant Deodorant Floral Bouquet

ACTIVE INGREDIENT

Aluminum Zirconium Pentachlorohydrex Gly 13.0%

PURPOSE

Antiperspirant

PURPOSE

Use......reduces underarm perspiration

WARNINGS

Warning...For external use only

Do not use on broken skin

Stop use and ask a doctor if rash or irritation occurs.

Keep out of reach of children. If swallowed, get medical help or contact a poison control center right away

Ask a doctor before use if you have kidney disease.

INACTIVE INGREDIENT

Inactive Ingredients: cyclomethicone, Stearyl alcohol, PPG-14 butyl ether, hydrogenated castor oil, myristyl myristate, silica dimethyl silylate, C20-40 pareth-10, fragrance, red 40 lake.

HOW SUPPLIED

The distinctive design and elements of this package are proprietary and owned by The Dial Corporation, A Henkel Company.

2010 Distributed by The Dial Corporation, A Henkel Company, Scottsdale, AZ, 85255. MADE IN CANADA

DOSAGE AND ADMINISTRATION

Directions: Apply to underarms only

INDICATIONS AND USAGE

Use: reduces underarm perspiration.